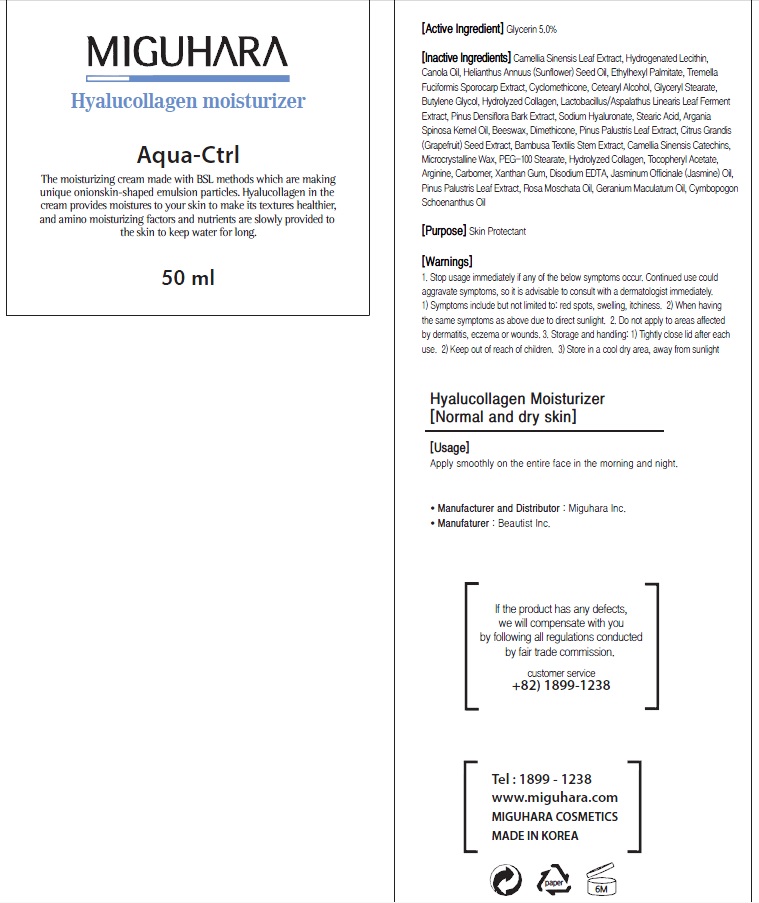 DRUG LABEL: Hyalucollagen Moisturizer
NDC: 70380-240 | Form: CREAM
Manufacturer: MIGUHARA
Category: otc | Type: HUMAN OTC DRUG LABEL
Date: 20160222

ACTIVE INGREDIENTS: Glycerin 2.5 g/50 mL
INACTIVE INGREDIENTS: GREEN TEA LEAF; HYDROGENATED SOYBEAN LECITHIN

ACTIVE INGREDIENT

Active Ingredient: Glycerin 5.0%

INACTIVE INGREDIENT

Inactive Ingredients: Camellia Sinensis Leaf Extract, Hydrogenated Lecithin, Canola Oil, Helianthus Annuus (Sunflower) Seed Oil, Ethylhexyl Palmitate, Tremella Fuciformis Sporocarp Extract, Cyclomethicone, Cetearyl Alcohol, Glyceryl Stearate, Butylene Glycol, Hydrolyzed Collagen, Lactobacillus/Aspalathus Linearis Leaf Ferment Extract, Pinus Densiflora Bark Extract, Sodium Hyaluronate, Stearic Acid, Argania Spinosa Kernel Oil, Beeswax, Dimethicone, Pinus Palustris Leaf Extract, Citrus Grandis (Grapefruit) Seed Extract, Bambusa Textilis Stem Extract, Camellia Sinensis Catechins, Microcrystalline Wax, PEG-100 Stearate, Hydrolyzed Collagen, Tocopheryl Acetate, Arginine, Carbomer, Xanthan Gum, Disodium EDTA, Jasminum Officinale (Jasmine) Oil, Pinus Palustris Leaf Extract, Rosa Moschata Oil, Geranium Maculatum Oil, Cymbopogon Schoenanthus Oil

PURPOSE

Purpose: Skin Protectant

WARNINGS

1. Stop usage immediately if any of the below symptoms occur. Continued use could aggravate symptoms, so it is advisable to consult with a dermatologist immediately. 1) Symptoms include but not limited to: red spots, swelling, itchiness. 2) When having the same symptoms as above due to direct sunlight. 2. Do not apply to areas affected by dermatitis, eczema or wounds. 3. Storage and handling: 1) Tightly close lid after each use. 2 Keep out of reach of children 3) Store in a cool dry area, away from sunlight

KEEP OUT OF REACH OF CHILDREN

Usage

Usage: Apply smoothly on the entire face in the morning and night.

Usage

Usage: Apply smoothly on the entire face in the morning and night.